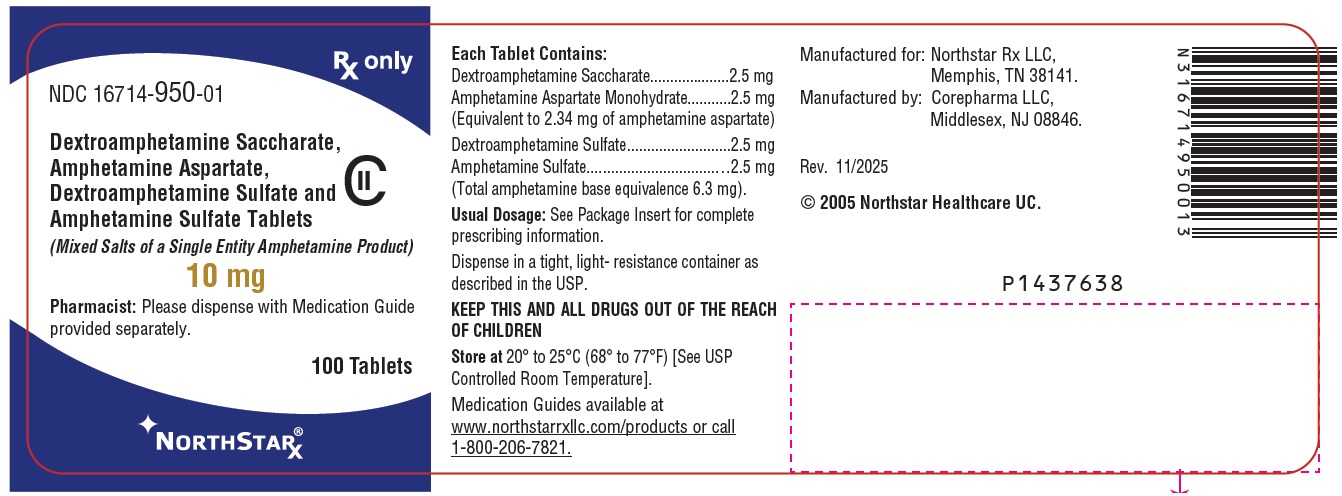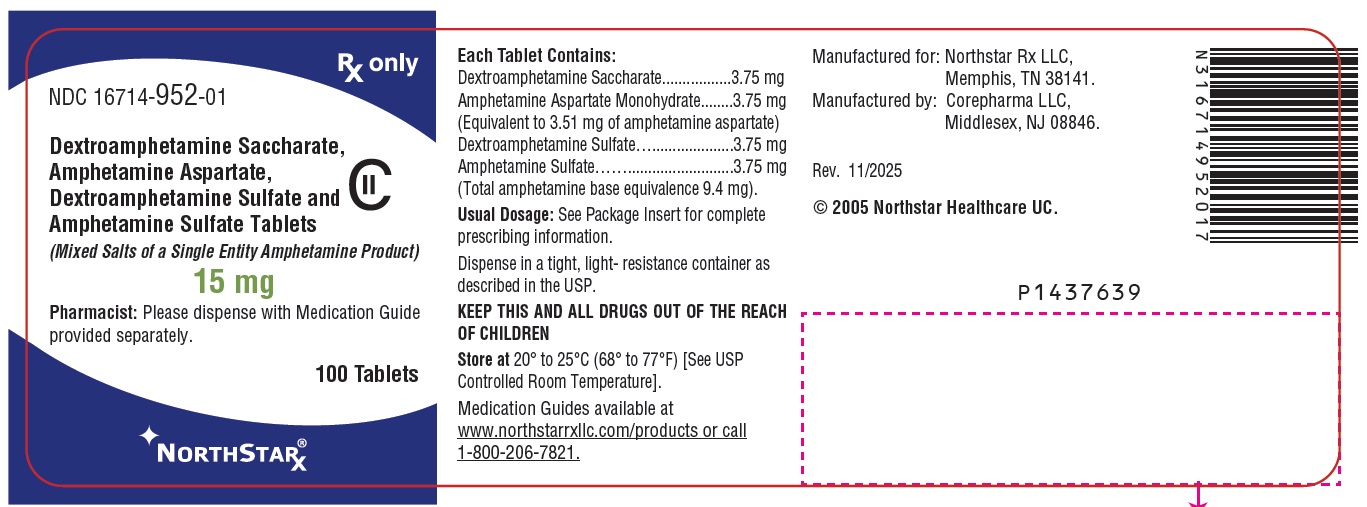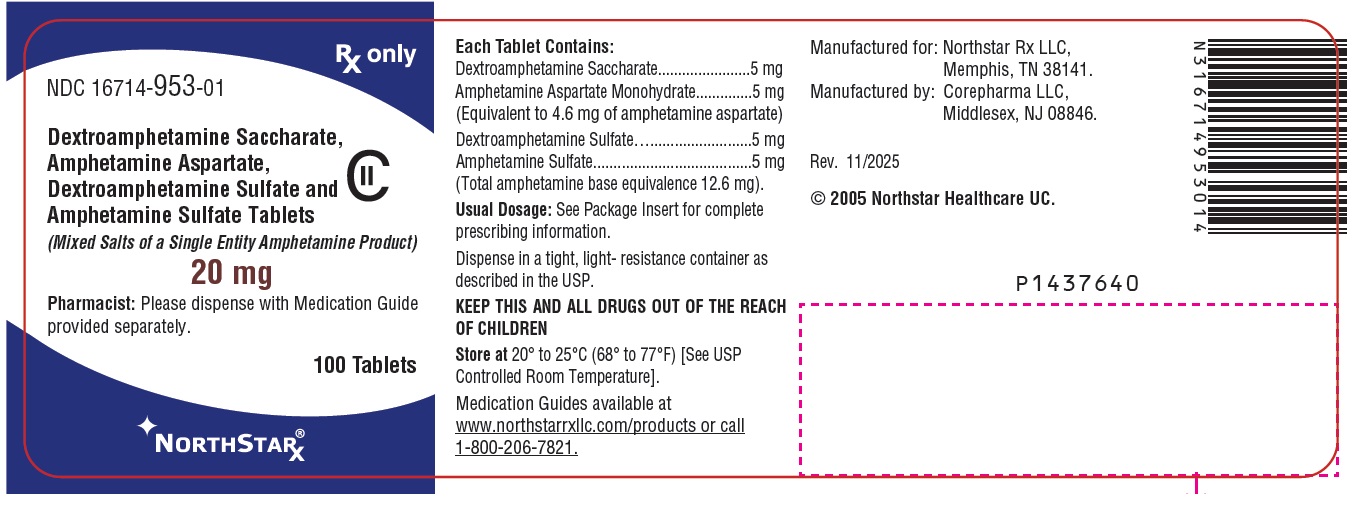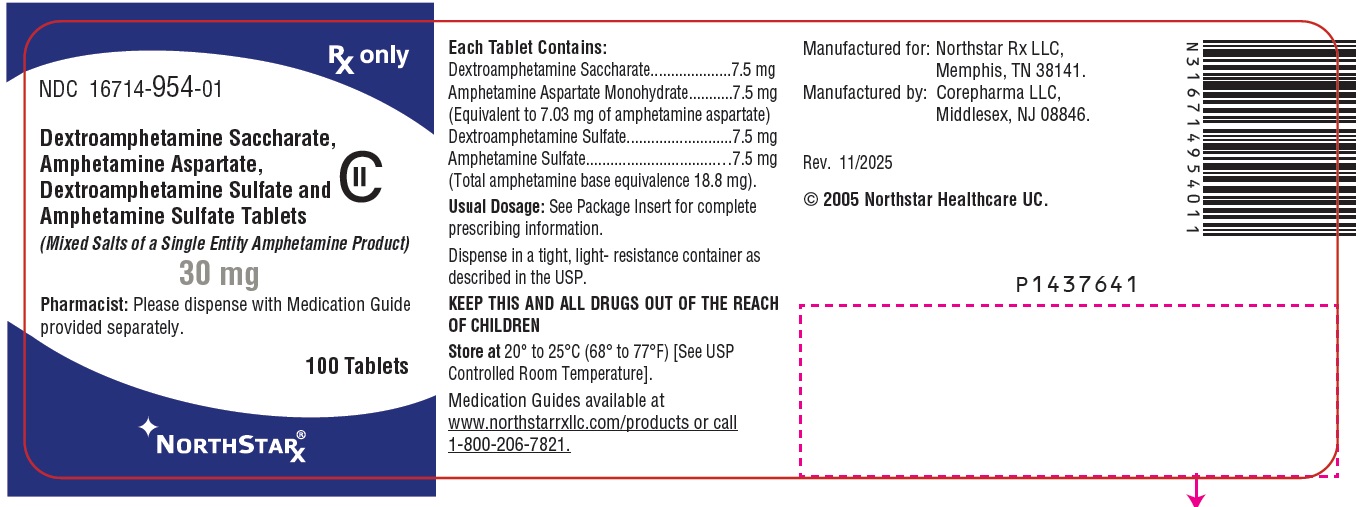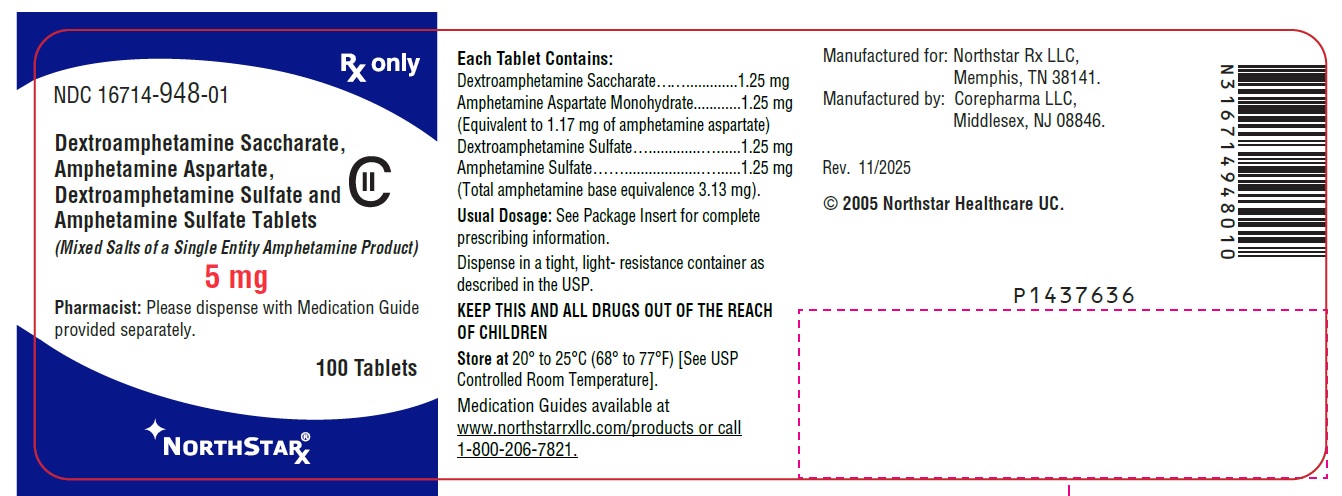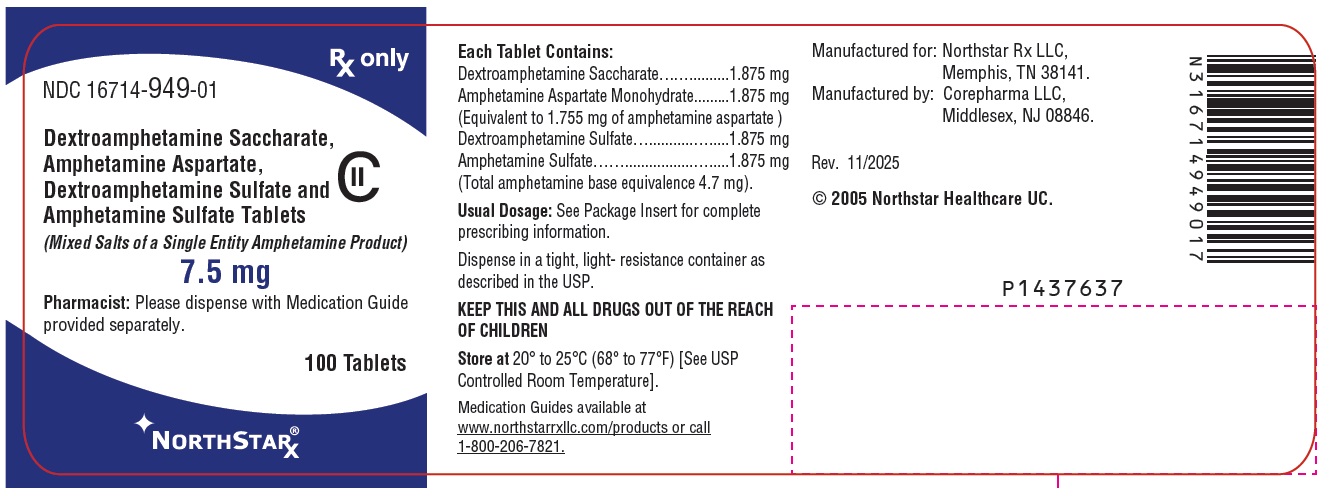 DRUG LABEL: Dextroamphetamine Saccharate, Amphetamine Aspartate, Dextroamphetamine Sulfate and Amphetamine Sulfate
NDC: 16714-948 | Form: TABLET
Manufacturer: NorthStar RxLLC
Category: prescription | Type: Human Prescription Drug Label
Date: 20251212
DEA Schedule: CII

ACTIVE INGREDIENTS: DEXTROAMPHETAMINE SACCHARATE 1.25 mg/1 1; AMPHETAMINE ASPARTATE MONOHYDRATE 1.25 mg/1 1; DEXTROAMPHETAMINE SULFATE 1.25 mg/1 1; AMPHETAMINE SULFATE 1.25 mg/1 1
INACTIVE INGREDIENTS: SILICON DIOXIDE; MAGNESIUM STEARATE; CELLULOSE, MICROCRYSTALLINE; POVIDONE; STARCH, CORN; FD&C BLUE NO. 1

Dextroamphetamine Saccharate, Amphetamine Aspartate, Dextroamphetamine Sulfate and Amphetamine Sulfate Tablets CII
Rx Only

BOXED WARNING

Dextroamphetamine saccharate, amphetamine aspartate, dextroamphetamine sulfate and amphetamine sulfate tablet has a high potential for abuse and misuse, which can lead to the development of a substance use disorder, including addiction. Misuse and abuse of CNS stimulants, including Dextroamphetamine Saccharate, Amphetamine Aspartate, Dextroamphetamine Sulfate and Amphetamine Sulfate Tablets, can result in overdose and death (see OVERDOSAGE), and this risk is increased with higher doses or unapproved methods of administration, such as snorting or injection.

Before prescribing Dextroamphetamine Saccharate, Amphetamine Aspartate, Dextroamphetamine Sulfate and Amphetamine Sulfate Tablets, assess each patient’s risk for abuse, misuse, and addiction. Educate patients and their families about these risks, proper storage of the drug, and proper disposal of any unused drug. Throughout Dextroamphetamine Saccharate, Amphetamine Aspartate, Dextroamphetamine Sulfate and Amphetamine Sulfate Tablets treatment, reassess each patient’s risk of abuse, misuse, and addiction and frequently monitor for signs and symptoms of abuse, misuse, and addiction (see WARNINGS and DRUG ABUSE AND DEPENDENCE).

DESCRIPTION

A single-entity amphetamine product combining the neutral sulfate salts of Dextroamphetamine and amphetamine, with the Dextro isomer of amphetamine Saccharate and d, 1-amphetamine aspartate.

EACH TABLET CONTAINS | 5 mg | 7.5 mg | 10 mg | 15 mg | 20 mg | 30 mg
Dextroamphetamine Saccharate | 1.25 mg | 1.875 mg | 2.5 mg | 3.75 mg | 5 mg | 7.5 mg
Amphetamine Aspartate Monohydrate Equivalent | 1.25 mg^1 | 1.875 mg^2 | 2.5 mg^3 | 3.75 mg^4 | 5 mg^5 | 7.5 mg^6
Dextroamphetamine Sulfate, USP | 1.25 mg | 1.875 mg | 2.5 mg | 3.75 mg | 5 mg | 7.5 mg
Amphetamine Sulfate, USP | 1.25 mg | 1.875 mg | 2.5 mg | 3.75 mg | 5 mg | 7.5 mg
Total Amphetamine Base Equivalence | 3.13 mg | 4.7 mg | 6.3 mg | 9.4 mg | 12.6 mg | 18.8 mg

^11.25 mg of Amphetamine Aspartate Monohydrate equivalent to 1.17 mg Amphetamine Aspartate (Anhydrous) as supplied
^21.875 mg of Amphetamine Aspartate Monohydrate equivalent to 1.755 mg Amphetamine Aspartate (Anhydrous) as supplied
^32.5 mg of Amphetamine Aspartate Monohydrate equivalent to 2.34 mg Amphetamine Aspartate (Anhydrous) as supplied
^43.75 mg of Amphetamine Aspartate Monohydrate equivalent to 3.51 mg Amphetamine Aspartate (Anhydrous) as supplied
^55 mg of Amphetamine Aspartate Monohydrate equivalent to 4.6 mg Amphetamine Aspartate (Anhydrous) as supplied
^67.5 mg of Amphetamine Aspartate Monohydrate equivalent to 7.03 mg Amphetamine Aspartate (Anhydrous) as supplied

Inactive Ingredients

In addition, each tablet contains: colloidal silicon dioxide, magnesium stearate, microcrystalline cellulose, povidone, and pregelatinized starch.

Colors

The 5 mg, 7.5 mg, and 10 mg tablets contain the color additive FD&C Blue #1 Aluminum Lake.

The 15 mg, 20 mg, and 30 mg tablets contain the color additive FD&C Yellow #6 Aluminum Lake.

CLINICAL PHARMACOLOGY

Pharmacodynamics

Amphetamines are non-catecholamine sympathomimetic amines with CNS stimulant activity. The mode of therapeutic action in Attention Deficit Hyperactivity Disorder (ADHD) is not known. Amphetamines are thought to block the reuptake of norepinephrine and dopamine into the presynaptic neuron and increase the release of these monoamines into the extra neuronal space.

Pharmacokinetics

Dextroamphetamine Saccharate, Amphetamine Aspartate, Dextroamphetamine Sulfate and Amphetamine Sulfate Tablets contain d-amphetamine and l-amphetamine salts in the ratio of 3:1. Following administration of a single dose 10 or 30 mg of Dextroamphetamine Saccharate, Amphetamine Aspartate, Dextroamphetamine Sulfate and Amphetamine Sulfate Tablets to healthy volunteers under fasted conditions, peak plasma concentrations occurred approximately 3 hours post-dose for both d-amphetamine and l-amphetamine. The mean elimination half-life (t1/2) for d-amphetamine was shorter than the t1/2 of the 1-isomer (9.77 to 11 hours vs. 11.5 to 13.8 hours). The PK parameters (Cmax, AUC0-inf) of d-and l -amphetamine increased approximately three-fold from 10 mg to 30 mg indicating dose-proportional pharmacokinetics.

The effect of food on the bioavailability of Dextroamphetamine Saccharate, Amphetamine Aspartate, Dextroamphetamine Sulfate and Amphetamine Sulfate Tablets has not been studied.

Metabolism and Excretion

Amphetamine is reported to be oxidized at the 4 position of the benzene ring to form 4- hydroxyamphetamine, or on the side chain α or β carbons to form alpha-hydroxy-amphetamine or norephedrine, respectively. Norephedrine and 4-hydroxy-amphetamine are both active and each is subsequently oxidized to form 4-hydroxy-norephedrine. Alpha-hydroxy-amphetamine undergoes deamination to form phenyl acetone, which ultimately forms benzoic acid and its glucuronide and the glycine conjugate hippuric acid. Although the enzymes involved in amphetamine metabolism have not been clearly defined, CYP2D6 is known to be involved with formation of 4-hydroxy-amphetamine. Since CYP2D6 is genetically polymorphic, population variations in amphetamine metabolism are a possibility.

Amphetamine is known to inhibit monoamine oxidase, whereas the ability of amphetamine and its metabolites to inhibit various P450 isozymes and other enzymes has not been adequately elucidated. In vitro experiments with human microsomes indicate minor inhibition of CYP2D6 by amphetamine and minor inhibition of CYP1A2, 2D6, and 3A4 by one or more metabolites. However, due to the probability of auto-inhibition and the lack of information on the concentration of these metabolites relative to in vivo concentrations, no predications regarding the potential for amphetamine or its metabolites to inhibit the metabolism of other drugs by CYP isozymes in vivo can be made.

With normal urine pHs approximately half of an administered dose of amphetamine is recoverable in urine as derivatives of alpha-hydroxy-amphetamine and approximately another 30% to 40% of the dose is recoverable in urine as amphetamine itself. Since amphetamine has a pKa of 9.9, urinary recovery of amphetamine is highly dependent on pH and urine flow rates. Alkaline urine pHs result in less ionization and reduced renal elimination, and acidic pHs and high flow rates result in increased renal elimination with clearances greater than glomerular filtration rates, indicating the involvement of active secretion. Urinary recovery of amphetamine has been reported to range from 1% to 75%, depending on urinary pH, with the remaining fraction of the dose hepatically metabolized. Consequently, both hepatic and renal dysfunction have the potential to inhibit the elimination of amphetamine and result in prolonged exposures. In addition, drugs that affect urinary pH are known to alter the elimination of amphetamine, and any decrease in amphetamine's metabolism that might occur due to drug interactions or genetic polymorphisms is more likely to be clinically significant when renal elimination is decreased [see PRECAUTIONS].

INDICATIONS AND USAGE

Dextroamphetamine Saccharate, Amphetamine Aspartate, Dextroamphetamine Sulfate and Amphetamine Sulfate Tablets are indicated for the treatment of Attention Deficit Hyperactivity Disorder (ADHD) and Narcolepsy.

Attention Deficit Hyperactivity Disorder (ADHD)

A diagnosis of Attention Deficit Hyperactivity Disorder (ADHD; DSM-IV®) implies the presence of hyperactive-impulsive or inattentive symptoms that caused impairment and were present before age 7 years. The symptoms must cause clinically significant impairment, e.g., in social, academic, or occupational functioning, and be present in two or more settings, e.g., school (or work) and at home. The symptoms must not be better accounted for by another mental disorder. For the Inattentive Type, at least six of the following symptoms must have persisted for at least 6 months: lack of attention to details/careless mistakes; lack of sustained attention; poor listener; failure to follow through on tasks; poor organization; avoids tasks requiring sustained mental effort; loses things; easily distracted; forgetful. For the Hyperactive-Impulsive Type, at least six of the following symptoms must have persisted for at least 6 months: fidgeting/squirming; leaving seat; inappropriate running/climbing; difficulty with quiet activities; "on the go;" excessive talking; blurting answers; can't wait turn; intrusive. The Combined Type requires both inattentive and hyperactive-impulsive criteria to be met.

CONTRAINDICATIONS

Advanced arteriosclerosis, symptomatic cardiovascular disease, moderate to severe hypertension, hyperthyroidism, known hypersensitivity or idiosyncrasy to the sympathomimetic amines, glaucoma.

Agitated states.

Known hypersensitivity or idiosyncrasy to amphetamine. Patients with a history of drug abuse.

In patients known to be hypersensitive to amphetamine, or other components of Dextroamphetamine Saccharate, Amphetamine Aspartate, Dextroamphetamine Sulfate and Amphetamine Sulfate Tablets . Hypersensitivity reactions such as angioedema and anaphylactic reactions have been reported in patients treated with other amphetamine products [seeADVERSE REACTIONS].

Patients taking monoamine oxidase inhibitors (MAOIs), or within 14 days of stopping MAOIs (including MAOIs such as linezolid or intravenous methylene blue), because of an increased risk of hypertensive crisis [seeWARNINGS andDRUG INTERACTIONS].

WARNINGS

Abuse, Misuse, and Addiction

Dextroamphetamine saccharate, amphetamine aspartate, dextroamphetamine sulfate and amphetamine sulfate tablets has a high potential for abuse and misuse. The use of Dextroamphetamine saccharate, amphetamine aspartate, dextroamphetamine sulfate and amphetamine sulfate tablets

exposes individuals to the risks of abuse and misuse, which can lead to the development of a substance use disorder, including addiction. Dextroamphetamine saccharate, amphetamine aspartate, dextroamphetamine sulfate and amphetamine sulfate tablets can be diverted for non-medical use into illicit channels or distribution (see DRUG ABUSE and DEPENDENCE: Abuse). Misuse and abuse of CNS stimulants, including Dextroamphetamine saccharate, amphetamine aspartate, dextroamphetamine sulfate and amphetamine sulfate tablets, can result in overdose and death (see OVERDOSAGE), and this risk is increased with higher doses or unapproved methods of administration, such as snorting or injection.

Before prescribing Dextroamphetamine saccharate, amphetamine aspartate, dextroamphetamine sulfate and amphetamine sulfate tablets, assess each patient’s risk for abuse, misuse, and addiction. Educate patients and their families about these risks and proper disposal of any unused drug. Advise patients to store amphetamine sulfate in a safe place, preferably locked, and instruct patients to not give Dextroamphetamine saccharate, amphetamine aspartate, dextroamphetamine sulfate and amphetamine sulfate tablets to anyone else. Throughout Dextroamphetamine saccharate, amphetamine aspartate, dextroamphetamine sulfate and amphetamine sulfate tablets treatment, reassess each patient’s risk of abuse, misuse, and addiction and frequently monitor for signs and symptoms of abuse, misuse, and addiction.

Risks to Patients with Serious Cardiac Disease

Sudden death has been reported in patients with structural cardiac abnormalities or other serious cardiac disease who were treated with CNS stimulant treatment at the recommended ADHD dosages.

Avoid Dextroamphetamine saccharate, amphetamine aspartate, dextroamphetamine sulfate and amphetamine sulfate tablets use in patients with known structural cardiac abnormalities, cardiomyopathy, serious cardiac arrhythmia, coronary artery disease, or other serious cardiac disease.

Increased Blood Pressure and Heart Rate

CNS stimulants cause an increase in blood pressure (mean increase about 2 to 4 mm Hg) and heart rate (mean increase about 3 to 6 bpm). Some patients may have larger increases. Monitor all Dextroamphetamine saccharate, amphetamine aspartate, dextroamphetamine sulfate and amphetamine sulfate tablets -treated patients for potential tachycardia and hypertension.

Psychiatric Adverse Reactions

Exacerbation of Pre Existing Psychosis

CNS stimulants may exacerbate symptoms of behavior disturbance and thought disorder in patients with a pre-existing psychotic disorder.

Induction of a Manic Episode in Patients with Bipolar Disorder

CNS stimulants may induce a manic or mixed episode in patients. Prior to initiating treatment, screen patients for risk factors for developing a manic episode (e.g., comorbid or history of depressive symptoms or a family history of suicide, bipolar disorder, or depression).

New Psychotic or Manic Symptoms

CNS stimulants, at recommended doses, may cause psychotic or manic symptoms (e.g., hallucinations, delusional thinking, or mania) in patients without a prior history of psychotic illness or mania. In a pooled analysis of multiple short-term, placebo-controlled studies of CNS stimulants, psychotic or manic symptoms

occurred in approximately 0.1% of CNS stimulant-treated patients, compared with 0% of placebo-treated patients. If such symptoms occur, consider discontinuing Dextroamphetamine saccharate, amphetamine aspartate, dextroamphetamine sulfate and amphetamine sulfate tablets.

Long-Term Suppression of Growth in Pediatric Patients

CNS stimulants have been associated with weight loss and slowing of growth rate in pediatric patients. Closely monitor growth (weight and height) in Dextroamphetamine saccharate, amphetamine aspartate, dextroamphetamine sulfate and amphetamine sulfate tablets treated pediatric patients treated with CNS stimulants. Pediatric patients who are not growing or gaining weight as expected may need to have their treatment interrupted (see PRECAUTIONS, PEDIATRIC USE).

Seizures

There is some clinical evidence that stimulants may lower the convulsive threshold in patients with prior history of seizure, in patients with prior EEG abnormalities in absence of seizures, and very rarely, in patients without a history of seizures and no prior EEG evidence of seizures. In the presence of seizures, the drug should be discontinued.

Peripheral Vasculopathy, Including Raynaud’s Phenomenon

Stimulants, including Dextroamphetamine saccharate, amphetamine aspartate, dextroamphetamine sulfate and amphetamine sulfate tablets, used to treat ADHD are associated with peripheral vasculopathy, including Raynaud’s phenomenon. Signs and symptoms are usually intermittent and mild; however, sequelae include digital ulceration and/or soft tissue breakdown. Effects of peripheral vasculopathy, including Raynaud’s phenomenon, were observed in postmarketing reports and at the therapeutic dosage of CNS stimulants in all age groups throughout the course of treatment. Signs and symptoms generally improved after dosage reduction or discontinuation of the CNS stimulant. Careful observation for digital changes is necessary during Dextroamphetamine saccharate, amphetamine aspartate, dextroamphetamine sulfate and amphetamine sulfate tablets treatment. Further clinical evaluation (e.g., rheumatology referral) may be appropriate for Dextroamphetamine saccharate, amphetamine aspartate, dextroamphetamine sulfate and amphetamine sulfate tablets treated certain patients who develop signs or symptoms of peripheral vasculopathy.

Serotonin Syndrome

Serotonin syndrome, a potentially life-threatening reaction, may occur when amphetamines are used in combination with other drugs that affect the serotonergic neurotransmitter systems such as monoamine oxidase inhibitors (MAOIs), selective serotonin reuptake inhibitors (SSRIs), serotonin norepinephrine reuptake inhibitors (SNRIs), triptans, tricyclic antidepressants, fentanyl, lithium, tramadol, tryptophan, buspirone, and St. John's Wort [see DRUG INTERACTIONS].

The co-administration with cytochrome P450 (CYP2D6) inhibitors increase the risk with increased exposure to Dextroamphetamine saccharate, amphetamine aspartate, dextroamphetamine sulfate and amphetamine sulfate tablets. In these situations, consider an alternative non-serotonergic drug or an alternative drug that does not inhibit CYP2D6 [see DRUG INTERACTIONS].

Serotonin syndrome symptoms may include mental status changes (e.g., agitation, hallucinations, delirium, and coma), autonomic instability (e.g., tachycardia, labile blood pressure, dizziness, diaphoresis, flushing, and hyperthermia), neuromuscular symptoms (e.g., tremor, rigidity, myoclonus, hyperreflexia, and incoordination), seizures, and/or gastrointestinal symptoms (e.g., nausea, vomiting, diarrhea).

Concomitant use of Dextroamphetamine saccharate, amphetamine aspartate, dextroamphetamine sulfate and amphetamine sulfate tablets with MAOIs drugs is contraindicated [see CONTRAINDICATIONS].

Discontinue treatment with Dextroamphetamine saccharate, amphetamine aspartate, dextroamphetamine sulfate and amphetamine sulfate tablets and any concomitant serotonergic agents immediately if the above symptoms occur and initiate supportive symptomatic treatment. If concomitant use Dextroamphetamine saccharate, amphetamine aspartate, dextroamphetamine sulfate and amphetamine sulfate tablets with other serotonergic drugs or CYP2D6 inhibitors is clinically warranted, initiate Dextroamphetamine saccharate, amphetamine aspartate, dextroamphetamine sulfate and amphetamine sulfate tablets with lower doses, monitor patients for the emergence of serotonin syndrome during drug initiation or titration, and inform patients of the increased risk for serotonin syndrome.

Motor and Verbal Tics, and Worsening of Tourette’s Syndrome

CNS stimulants, including amphetamine sulfate, have been associated with the onset or exacerbation of motor and verbal tics. Worsening of Tourette’s syndrome has also been reported. Before initiating Dextroamphetamine Saccharate, Amphetamine Aspartate, Dextroamphetamine Sulfate and Amphetamine Sulfate Tablets, assess the family history and clinically evaluate patients for tics or Tourette’s syndrome. Regularly monitor patients for the emergence or worsening of tics or Tourette’s syndrome with Dextroamphetamine Saccharate, Amphetamine Aspartate, Dextroamphetamine Sulfate and Amphetamine Sulfate Tablets and discontinue treatment if clinically appropriate.

PRECAUTIONS

Information for Patients

Advise the patient to read the FDA-approved patient labeling (Medication Guide).

Abuse, Misuse, and Addiction

Educate patients and their families about the risks of abuse, misuse, and addiction of Dextroamphetamine saccharate, amphetamine aspartate, dextroamphetamine sulfate and amphetamine sulfate tablets, which can lead to overdose and death, and proper disposal of any unused drug [see WARNINGS, DRUG ABUSE AND DEPENDENCE, OVERDOSAGE]. Advise patients to store Dextroamphetamine saccharate, amphetamine aspartate, dextroamphetamine sulfate and amphetamine sulfate tablets in a safe place, preferably locked, and instruct patients to not give Dextroamphetamine saccharate, amphetamine aspartate, dextroamphetamine sulfate and amphetamine sulfate tablets to anyone else.

Risks to Patients with Serious Cardiac Disease

Advise patients that there are potential risks to patients with serious cardiac disease, including sudden death, with Dextroamphetamine saccharate, amphetamine aspartate, dextroamphetamine sulfate and amphetamine sulfate tablets use. Instruct patients to contact a healthcare provider immediately if they develop symptoms such as exertional chest pain, unexplained syncope, or other symptoms suggestive of cardiac disease [see WARNINGS].

Increased Blood Pressure and Heart Rate

Advise patients that Dextroamphetamine saccharate, amphetamine aspartate, dextroamphetamine sulfate and amphetamine sulfate tablets can elevate blood pressure and heart rate [see WARNINGS].

Psychiatric Adverse Reactions

Advise patients that Dextroamphetamine saccharate, amphetamine aspartate, dextroamphetamine sulfate and amphetamine sulfate tablets, at recommended doses, can cause psychotic or manic symptoms, even in patients without prior history of psychotic symptoms or mania [see WARNINGS].

Long-Term Suppression of Growth in Pediatric Patients

Advise patients that Dextroamphetamine saccharate, amphetamine aspartate, dextroamphetamine sulfate and amphetamine sulfate tablets may cause slowing of growth including weight loss [see WARNINGS].

Circulation Problems in Fingers and Toes [Peripheral Vasculopathy, Including Raynaud’s Phenomenon]

- Instruct patients beginning treatment with dextroamphetamine saccharate, aspartate, dextroamphetamine sulfate and amphetamine sulfate tablets, about the risk of peripheral Vasculopathy, including Raynaud’s phenomenon, and associated signs and symptoms: fingers or toes may feel numb, cool, painful, and/or may change color from pale, to blue, to red.
- Instruct patients to report to their physician any new numbness, pain, skin color change, or sensitivity to temperature in fingers or toes.
- Instruct patients to call their physician immediately with any signs of unexplained wounds appearing on fingers or toes while taking dextroamphetamine saccharate, amphetamine aspartate monohydrate, dextroamphetamine sulfate and amphetamine sulfate tablets.
- Further clinical evaluation (e.g., rheumatology referral) may be appropriate for certain patients.

Serotonin Syndrome

Caution patients about the risk of serotonin syndrome with concomitant use of dextroamphetamine saccharate, amphetamine aspartate, dextroamphetamine sulfate, and amphetamine sulfate tablets and other serotonergic drugs including SSRIs, SNRIs, triptans, tricyclic antidepressants, fentanyl, lithium, tramadol, tryptophan, buspirone, St. John's Wort, and with drugs that impair metabolism of serotonin (in particular MAOIs, both those intended to treat psychiatric disorders and also others such as linezolid [see CONTRAINDICATIONS, WARNINGS, and DRUG INTERACTIONS].

Advise patients to contact their healthcare provider or report to the emergency room if they experience signs or symptoms of serotonin syndrome.

Motor and Verbal Tics, and Worsening of Tourette’s Syndrome

• Advise patients that motor and verbal tics and worsening of Tourette’s Syndrome may occur during treatment with Dextroamphetamine saccharate, amphetamine aspartate, dextroamphetamine sulfate and amphetamine sulfate tablets. Instruct the patients to notify their healthcare provider if emergence or worsening of tics or Tourette’s syndrome occurs [see WARNINGS].

Drug Interactions

MAO Inhibitors

Concomitant use of MAOIs and CNS stimulants can cause hypertensive crisis. Potential outcomes include death, stroke, myocardial infarction, aortic dissection, ophthalmological complications, eclampsia, pulmonary edema, and renal failure. Do not administer Dextroamphetamine saccharate, amphetamine aspartate, dextroamphetamine sulfate and amphetamine sulfate tablets concomitantly or within 14 days after discontinuing MAOI [see CONTRAINDICATIONS and WARNINGS].

Serotonergic Drugs

The concomitant use of Dextroamphetamine saccharate, amphetamine aspartate, dextroamphetamine sulfate and amphetamine sulfate tablets and serotonergic drugs increases the risk of serotonin syndrome. Initiate with lower doses and monitor patients for signs and symptoms of serotonin syndrome, particularly during Dextroamphetamine saccharate, amphetamine aspartate, dextroamphetamine sulfate and amphetamine sulfate tablets initiation or dosage increase. If serotonin syndrome occurs, discontinue Dextroamphetamine saccharate, amphetamine aspartate, dextroamphetamine sulfate and amphetamine sulfate tablets and the concomitant serotonergic drug(s) [see WARNINGS and PRECAUTIONS].

CYP2D6 Inhibitors

The concomitant use of Dextroamphetamine saccharate, amphetamine aspartate, dextroamphetamine sulfate and amphetamine sulfate tablets and CYP2D6 inhibitors may increase the exposure of Dextroamphetamine saccharate, amphetamine aspartate, dextroamphetamine sulfate and amphetamine sulfate tablets compared to the use of the drug alone and increase the risk of serotonin syndrome. Initiate with lower doses and monitor patients for signs and symptoms of serotonin syndrome particularly during Dextroamphetamine saccharate, amphetamine aspartate, dextroamphetamine sulfate and amphetamine sulfate tablets initiation and after a dosage increase. If serotonin syndrome occurs, discontinue Dextroamphetamine saccharate, amphetamine aspartate, dextroamphetamine sulfate and amphetamine sulfate tablets and the CYP2D6 inhibitor [see WARNINGS, OVERDOSAGE].

Acidifying agents

Lower blood levels and efficacy of amphetamines. Increase dose based on clinical response. Examples of acidifying agents include gastrointestinal acidifying agents and urinary acidifying agents.

Adrenergic Blockers

Adrenergic blockers are inhibited by amphetamines.

Alkalinizing Agents

Increase blood levels and potentiate the action of amphetamine. Co-administration of Dextroamphetamine saccharate, amphetamine aspartate, dextroamphetamine sulfate and amphetamine sulfate tablets and gastrointestinal alkalinizing agents should be avoided. Examples of alkalinizing agents include gastrointestinal alkalinizing agents (e.g., sodium bicarbonate) and urinary alkalinizing agents.

Tricyclic Antidepressants

May enhance the activity of tricyclic or sympathomimetic agents causing striking and sustained increases in the concentration of d-amphetamine in the brain; cardiovascular effects can be potentiated. Monitor frequently and adjust or use alternative therapy based on clinical response.

Antihistamines

Amphetamines may counteract the sedative effect of antihistamines.

Antihypertensives

Amphetamines may antagonize the hypotensive effects of antihypertensives.

Chlorpromazine

Chlorpromazine blocks dopamine and norepinephrine receptors, thus inhibiting the central stimulant effects of amphetamines, and can be used to treat amphetamine poisoning.

Ethosuximide

Amphetamines may delay intestinal absorption of ethosuximide.

Haloperidol

Haloperidol blocks dopamine receptors, thus inhibiting the central stimulant effects of amphetamines.

Lithium Carbonate

The anorectic and stimulatory effects of amphetamines may be inhibited by lithium carbonate.

Meperidine

Amphetamines potentiate the analgesic effect of meperidine.

Methenamine Therapy

Urinary excretion of amphetamines is increased, and efficacy is reduced, by acidifying agents used in

methenamine therapy.

Norepinephrine

Amphetamines enhance the adrenergic effect of norepinephrine.

Phenobarbital

Amphetamines may delay intestinal absorption of phenobarbital; coadministration of phenobarbital may produce a synergistic anticonvulsant action.

Phenytoin

Amphetamines may delay intestinal absorption of phenytoin; coadministration of phenytoin may produce a synergistic anticonvulsant action.

Propoxyphene

In cases of propoxyphene overdosage, amphetamine CNS stimulation is potentiated and fatal convulsions can occur.

Proton Pump Inhibitors

Time to maximum concentration (Tmax) of amphetamine is decreased compared to when administered alone. Monitor patients for changes in clinical effect and adjust therapy based on clinical response. An example of a proton pump inhibitor is omeprazole.

Veratrum Alkaloids

Amphetamines inhibit the hypotensive effect of veratrum alkaloids.

Drug/Laboratory Test Interactions

Amphetamines can cause a significant elevation in plasma corticosteroid levels. This increase is greatest in the evening. Amphetamines may interfere with urinary steroid determinations.

Carcinogenesis, Mutagenesis, Impairment of Fertility

No evidence of carcinogenicity was found in studies in which d,l-amphetamine (enantiomer ratio of 1:1) was administered to mice and rats in the diet for 2 years at doses of up to 30 mg/kg/day in male mice, 19 mg/kg/day in female mice, and 5 mg/kg/day in male and female rats. These doses are approximately 2.4, 1.5, and 0.8 times, respectively, the maximum recommended human dose of 30 mg/day [child] on a mg/m2 body surface area basis.

Amphetamine, in the enantiomer ratio present in dextroamphetamine saccharate, amphetamine aspartate, dextroamphetamine sulfate and amphetamine sulfate tablets (immediate-release)(d- to l- ratio of 3:1), was not clastogenic in the mouse bone marrow micronucleus test in vivo and was negative when tested in the E. coli component of the Ames test in vitro. d, l-Amphetamine (1:1 enantiomer ratio) has been reported to produce a positive response in the mouse bone marrow micronucleus test, an equivocal response in the Ames test, and negative responses in the in vitro sister chromatid exchange and chromosomal aberration assays.

Amphetamine, in the enantiomer ratio present in dextroamphetamine saccharate, amphetamine aspartate, dextroamphetamine sulfate and amphetamine sulfate tablets (immediate-release)(d- to l- ratio of 3:1), did not adversely affect fertility or early embryonic development in the rat at doses of up to 20 mg/kg/day (approximately 5 times the maximum recommended human dose of 30 mg/day on a mg/m2 body surface area basis).

Pregnancy

Teratogenic Effects

Amphetamine, in the enantiomer ratio present in dextroamphetamine saccharate, amphetamine aspartate, dextroamphetamine sulfate and amphetamine sulfate tablets (d- to l- ratio of 3:1), had no apparent effects on embryofetal morphological development or survival when orally administered to pregnant rats and rabbits throughout the period of organogenesis at doses of up to 6 and 16 mg/kg/day, respectively. These doses are approximately 1.5 and 8 times, respectively, the maximum recommended human dose of 30 mg/day [child] on a mg/m2 body surface area basis. Fetal malformations and death

have been reported in mice following parenteral administration of d-amphetamine doses of 50 mg/kg/day (approximately 6 times that of a human dose of 30 mg/day [child] on a mg/m2 basis) or greater to pregnant animals. Administration of these doses was also associated with severe maternal toxicity.

A number of studies in rodents indicate that prenatal or early postnatal exposure to amphetamine (d- or d,l-), at doses similar to those used clinically, can result in long-term neurochemical and behavioral alterations. Reported behavioral effects include learning and memory deficits, altered locomotor activity, and changes in sexual function.

There are no adequate and well-controlled studies in pregnant women. There has been one report of severe congenital bony deformity, tracheo-esophageal fistula, and anal atresia (vater association) in a baby born to a woman who took dextroamphetamine sulfate with lovastatin during the first trimester of pregnancy. Amphetamines should be used during pregnancy only if the potential benefit justifies the potential risk to the fetus.

Nonteratogenic Effects

Infants born to mothers dependent on amphetamines have an increased risk of premature delivery and low birth weight. Also, these infants may experience symptoms of withdrawal as demonstrated by dysphoria, including agitation, and significant lassitude.

Usage in Nursing Mothers

Amphetamines are excreted in human milk. Mothers taking amphetamines should be advised to refrain from nursing.

Pediatric Use

Long-term effects of amphetamines in children have not been well established. Amphetamines are not recommended for use in children under 3 years of age with Attention Deficit Hyperactivity Disorder described under INDICATIONS AND USAGE.

Geriatric Use

Dextroamphetamine saccharate, amphetamine aspartate, dextroamphetamine sulfate and amphetamine sulfate tablets have not been studied in the geriatric population.

ADVERSE REACTIONS

Cardiovascular

Palpitations, tachycardia, elevation of blood pressure, sudden death, myocardial infarction. There have been isolated reports of cardiomyopathy associated with chronic amphetamine use.

Central Nervous System

Psychotic episodes at recommended doses, overstimulation, restlessness, irritability, euphoria, dyskinesia, dysphoria, depression, tremor, motor and verbal tics, aggression, anger, logorrhea, dermatillomania.

Eye Disorders

Vision blurred, mydriasis.

Gastrointestinal

Dryness of the mouth, unpleasant taste, diarrhea, constipation, intestinal ischemia, other gastrointestinal disturbances. Anorexia and weight loss may occur as undesirable effects.

Allergic

Urticaria, rash, hypersensitivity reactions including angioedema and anaphylaxis. Serious skin rashes, including Stevens-Johnson syndrome and toxic epidermal necrolysis have been reported.

Endocrine

Impotence, changes in libido, frequent or prolonged erections.
Skin

Alopecia.

Musculoskeletal

Rhabdomyolysis.

DRUG ABUSE AND DEPENDENCE

Controlled Substance

Dextroamphetamine saccharate, amphetamine aspartate, dextroamphetamine sulfate and amphetamine sulfate tablets a Schedule II controlled substances.

Abuse

Dextroamphetamine saccharate, amphetamine aspartate, dextroamphetamine sulfate and amphetamine sulfate tablets has a high potential for abuse and misuse which can lead to the development of a substance use disorder, including addiction [see WARNINGS and PRECAUTIONS]. Dextroamphetamine saccharate, amphetamine aspartate , dextroamphetamine sulfate and amphetamine sulfate tablets can be diverted for non-medical use into illicit channels or distribution.

Abuse is the intentional non-therapeutic use of a drug, even once, to achieve a desired psychological or physiological effect. Misuse is the intentional use, for therapeutic purposes, of a drug by an individual in a way other than prescribed by a health care provider or for whom it was not prescribed. Drug addiction is a cluster of behavioral, cognitive, and physiological phenomena that may include a strong desire to take the drug, difficulties in controlling drug use (e.g., continuing drug use despite harmful consequences, giving a higher priority to drug use than other activities and obligations), and possible tolerance or physical dependence.

Misuse and abuse of amphetamines may cause increased heart rate, respiratory rate, or blood pressure; sweating; dilated pupils; hyperactivity; restlessness; insomnia; decreased appetite; loss of coordination; tremors; flushed skin; vomiting; and/or abdominal pain. Anxiety, psychosis, hostility, aggression, and suicidal or homicidal ideation have also been observed with CNS stimulants abuse and/or misuse. Misuse and abuse of CNS stimulants, including Dextroamphetamine saccharate, amphetamine aspartate, dextroamphetamine sulfate and amphetamine sulfate, can result in overdose and death [see OVERDOSAGE], and this risk is increased with higher doses or unapproved methods of administration, such as snorting or injection.

Dependence

Physical Dependence

Dextroamphetamine saccharate, amphetamine aspartate, dextroamphetamine sulfate and amphetamine sulfate may produce physical dependence. Physical dependence is a state that develops as a result of physiological adaptation in response to repeated drug use, manifested by withdrawal signs and symptoms after abrupt discontinuation or a significant dose reduction of a drug.

Withdrawal signs and symptoms after abrupt discontinuation or dose reduction following prolonged use of CNS stimulants including Dextroamphetamine saccharate, amphetamine aspartate, dextroamphetamine sulfate and amphetamine sulfate include dysphoric mood; depression; fatigue; vivid, unpleasant dreams; insomnia or hypersomnia; increased appetite; and psychomotor retardation or agitation.

Tolerance

Dextroamphetamine saccharate, amphetamine aspartate, dextroamphetamine sulfate and amphetamine sulfate may produce tolerance. Tolerance is a physiological state characterized by a reduced response to a drug after repeated administration (i.e., a higher dose of a drug is required to produce the same effect that was once obtained at a lower dose).

OVERDOSAGE

Clinical Effects of Overdose

Overdose of CNS stimulants is characterized by the following sympathomimetic effects:

• Cardiovascular effects including tachyarrhythmias, and hypertension or hypotension.

Vasospasm, myocardial infarction, or aortic dissection may precipitate sudden cardiac death. Takotsubo cardiomyopathy may develop.

• CNS effects including psychomotor agitation, confusion, and hallucinations. Serotonin syndrome, seizures, cerebral vascular accidents, and coma may occur.

• Life-threatening hyperthermia (temperatures greater than 104°F) and rhabdomyolysis may develop.

Overdose Management

Consider the possibility of multiple drug ingestion. D-amphetamine is not dialyzable. Consider contacting the Poison Help line (1-800-222-1222) or a medical toxicologist for additional overdose management recommendations.

DOSAGE & ADMINISTRATION

Regardless of indication, amphetamines should be administered at the lowest effective dosage and dosage should be individually adjusted according to the therapeutic needs and response of the patient. Late evening doses should be avoided because of the resulting insomnia.

Attention Deficit Hyperactivity Disorder

Not recommended for children under 3 years of age. In children from 3 to 5 years of age, start with 2.5 mg daily; daily dosage may be raised in increments of 2.5 mg at weekly intervals until optimal response is obtained.

In children 6 years of age and older, start with 5 mg once or twice daily; daily dosage may be raised in increments of 5 mg at weekly intervals until optimal response is obtained. Only in rare cases will it be necessary to exceed a total of 40 mg per day. Give first dose on awakening; additional doses (1 or 2) at intervals of 4 to 6 hours.

Where possible, drug administration should be interrupted occasionally to determine if there is a recurrence of behavioral symptoms sufficient to require continued therapy.

Prior to treating patients with Dextroamphetamine saccharate, amphetamine aspartate, dextroamphetamine sulfate and amphetamine sulfate, assess:

• for the presence of cardiac disease (i.e., perform a careful history, family history of

sudden death or ventricular arrhythmia, and physical exam) (see WARNINGS).

• the family history and clinically evaluate patients for motor or verbal tics or Tourette’s

syndrome before initiating Dextroamphetamine saccharate, amphetamine aspartate, dextroamphetamine sulfate and amphetamine sulfate (see WARNINGS).

Narcolepsy

Usual dose 5 mg to 60 mg per day in divided doses, depending on the individual patient response.

Narcolepsy seldom occurs in children under 12 years of age; however, when it does, dextroamphetamine sulfate may be used. The suggested initial dose for patients aged 6 to 12 is 5 mg daily; daily dose may be raised in increments of 5 mg at weekly intervals until optimal response is obtained. In patients 12 years of age and older, start with 10 mg daily; daily dosage may be raised in increments of 10 mg at weekly intervals until optimal response is obtained. If bothersome adverse reactions appear (e.g., insomnia or anorexia), dosage should be reduced. Give first dose on awakening; additional doses (1 or 2) at intervals of 4 to 6 hours.

HOW SUPPLIED

Dextroamphetamine Saccharate, amphetamine aspartate, Dextroamphetamine sulfate and amphetamine sulfate tablets are supplied as:

5 mg Tablets - Light blue to blue colored, mottled, round, flat-faced, beveled edge tablets debossed with ‘U25’ on one side and quadrisect on other side.

Bottles of 100 16714-948-01

7.5 mg Tablets - Light blue to blue colored, mottled, round, convex tablets debossed with ‘U26’ on one side and quadrisect on other side.

Bottles of 100 16714-949-01

10 mg Tablets - Light blue to blue colored, mottled, round, convex tablets debossed with ‘U27’ on one side and quadrisect on other side.

Bottles of 100 16714-950-01

15 mg Tablets - Light orange to orange colored, mottled, round, convex tablets debossed with ‘U29’ on one side and quadrisect on other side.

Bottles of 100 16714-952-01

20 mg Tablets - Light orange to orange colored, mottled, round, convex tablets debossed with ‘U30’ on one side and quadrisect on other side.

Bottles of 100 16714-953-01

30 mg Tablets - are light orange to orange colored, mottled, round, flat-faced, beveled edge tablets debossed with ‘U31’ on one side and quadrisect on other side.

Bottles of 100 16714-954-01

Dispense in a tight, light-resistant container as described in the USP.
KEEP THIS AND ALL DRUGS OUT OF THE REACH OF CHILDREN.
Store at 20° to 25°C (68° to 77°F) [See USP Controlled Room Temperature].
Dispense with Medication Guide available at www.northstarrxllc.com/products or call 1-800-206-7821

Manufactured for:
Northstar Rx LLC, Memphis, TN 38141.

Manufactured by:
Corepharma LLC, Middlesex, NJ 08846
Issued: 02/2025

MEDICATION GUIDE

Dextroamphetamine Saccharate, Amphetamine Aspartate, Dextroamphetamine Sulfate and Amphetamine Sulfate Tablets CII

(dex’’ troe am fet’ a meen sak’ a rate, am fet’ a meen as par’ tate, dex’’ troe am fet’ a meen sul’ fate, and am fet’ a meen sul’ fate)

What is the most important information I should know about Dextroamphetamine Saccharate, Amphetamine Aspartate, Dextroamphetamine Sulfate and Amphetamine Sulfate Tablets?

Dextroamphetamine Saccharate, Amphetamine Aspartate, Dextroamphetamine Sulfate and Amphetamine Sulfate Tablets may cause serious side effects, including:

• Abuse, misuse, and addiction. Dextroamphetamine Saccharate, Amphetamine Aspartate, Dextroamphetamine Sulfate and Amphetamine Sulfate Tablet has a high chance for abuse and misuse and may lead to substance use problems, including addiction. Misuse and abuse of Dextroamphetamine Saccharate, Amphetamine Aspartate, Dextroamphetamine Sulfate and Amphetamine Sulfate Tablets, other amphetamine containing medicines, and methylphenidate containing medicines, can lead to overdose and death. The risk of overdose and death is increased with higher doses of Dextroamphetamine Saccharate, Amphetamine Aspartate, Dextroamphetamine Sulfate and Amphetamine Sulfate Tablets or when it is used in ways that are not approved, such as snorting or injection.

- Your healthcare provider should check you or your child’s risk for abuse, misuse, and addiction before starting treatment with Dextroamphetamine Saccharate, Amphetamine Aspartate, Dextroamphetamine Sulfate and Amphetamine Sulfate Tablets and will monitor you or your child during treatment.
- Dextroamphetamine Saccharate, Amphetamine Aspartate, Dextroamphetamine Sulfate and Amphetamine Sulfate Tablets may lead to physical dependence after prolonged use, even if taken as directed by your healthcare provider. Do not give Dextroamphetamine Saccharate, Amphetamine Aspartate, Dextroamphetamine Sulfate and Amphetamine Sulfate Tablets to anyone else. See “What is Dextroamphetamine Saccharate, Amphetamine Aspartate, Dextroamphetamine Sulfate and Amphetamine Sulfate Tablets?” for more information.
- Keep Dextroamphetamine Saccharate, Amphetamine Aspartate, Dextroamphetamine Sulfate and Amphetamine Sulfate Tablets in a safe place and properly dispose of any unused medicine. See “How should I store Dextroamphetamine Saccharate, Amphetamine Aspartate, Dextroamphetamine Sulfate and Amphetamine Sulfate Tablets?” for more information.
- Tell your healthcare provider if you or your child have ever abused or been dependent on alcohol, prescription medicines, or street drugs.
- Risks for people with serious heart disease: Sudden death has happened in people who have heart defects or other serious heart disease.

Your healthcare provider should check you or your child carefully for heart problems before starting treatment with Dextroamphetamine Saccharate, Amphetamine Aspartate, Dextroamphetamine Sulfate and Amphetamine Sulfate Tablets. Tell your healthcare provider if you or your child have any heart problems, heart disease, or heart defects.

Call your healthcare provider right away or go to the nearest hospital emergency room right away if you or your child have any signs of heart problems such as chest pain, shortness of breath, or fainting during treatment with Dextroamphetamine Saccharate, Amphetamine Aspartate, Dextroamphetamine Sulfate and Amphetamine Sulfate Tablets.

• Increased blood pressure and heart rate.

Your healthcare provider should check you or your child’s blood pressure and heart rate regularly during treatment with Dextroamphetamine Saccharate, Amphetamine Aspartate, Dextroamphetamine Sulfate and Amphetamine Sulfate Tablets.

• Mental (psychiatric) problems, including:

- All Patients
- new or worse behavior and thought problems
- new or worse bipolar illness
- new psychotic symptoms (such as hearing voices, or seeing or believing things that are not real) or new manic symptoms

Tell your healthcare provider about any mental problems you or your child have, or about a family history of suicide, bipolar illness, or depression.

Call your healthcare provider right away if you or your child have any new or worsening mental symptoms or problems during treatment with Dextroamphetamine Saccharate, Amphetamine Aspartate, Dextroamphetamine Sulfate and Amphetamine Sulfate Tablets, especially hearing voices, seeing or believing things that are not real, or new manic symptoms.

What is Dextroamphetamine Saccharate, Amphetamine Aspartate, Dextroamphetamine Sulfate and Amphetamine Sulfate Tablets?

Dextroamphetamine saccharate, amphetamine aspartate, dextroamphetamine sulfate, and amphetamine sulfate tablets is a central nervous system (CNS) stimulant prescription medicine used for the treatment of:

- Attention-Deficit Hyperactivity Disorder (ADHD) in children 3 to 17 years of age. Dextroamphetamine saccharate, amphetamine aspartate, dextroamphetamine sulfate, and amphetamine sulfate tablets may help increase attention and decrease impulsiveness and hyperactivity in people with ADHD.
- A sleep disorder called Narcolepsy in people 6 years and older.

It is not known if Dextroamphetamine saccharate, amphetamine aspartate, dextroamphetamine sulfate, and amphetamine sulfate tablets is safe and effective in children with ADHD under 3 years of age.
It is not known if Dextroamphetamine saccharate, amphetamine aspartate, dextroamphetamine sulfate, and amphetamine sulfate tablets is safe and effective in children with Narcolepsy under 6 years of age.Dextroamphetamine saccharate, amphetamine aspartate, dextroamphetamine sulfate, and amphetamine sulfate tablets is a federally controlled substance (CII) because it contains amphetamine that can be a target for people who abuse prescription medicines or street drugs. Keep Dextroamphetamine saccharate, amphetamine aspartate, dextroamphetamine sulfate, and amphetamine sulfate tablets a safe place to protect it from theft. Never give your Dextroamphetamine saccharate, amphetamine aspartate, dextroamphetamine sulfate, and amphetamine sulfate tablets to anyone else because it may cause death or harm them. Selling or giving away Dextroamphetamine saccharate, amphetamine aspartate, dextroamphetamine sulfate, and amphetamine sulfate tablets may harm others and is against the law.

Do not take Dextroamphetamine Saccharate, Amphetamine Aspartate, Dextroamphetamine Sulfate and Amphetamine Sulfate Tablets if you or your child:

- are allergic to amphetamine products or any of the ingredients in Dextroamphetamine Saccharate, Amphetamine Aspartate, Dextroamphetamine Sulfate and Amphetamine Sulfate Tablets. See the end of this Medication Guide for a complete list of ingredients in Dextroamphetamine Saccharate, Amphetamine Aspartate, Dextroamphetamine Sulfate and Amphetamine Sulfate Tablets.
- are taking or have taken within the past 14 days, a medicine used to treat depression called a monoamine oxidase inhibitor or (MAOI), including the antibiotic linezolid or the intravenous medicine methylene blue.

Before taking Dextroamphetamine Saccharate, Amphetamine Aspartate, Dextroamphetamine Sulfate and Amphetamine Sulfate Tablets, tell your healthcare provider about all of your or your child’s medical conditions, including if you or your child:

- have heart problems, heart disease, heart defects, or high blood pressure
- have mental problems including psychosis, mania, bipolar illness, or depression, or have a family history of suicide, bipolar illness, or depression
- have kidney problems
- have seizures or have had an abnormal brain wave test (EEG)
- have circulation problems in fingers or toes
- have or had repeated movements or sounds (tics) or Tourette’s syndrome, or have a family history of tics or Tourette’s syndrome
- are pregnant or plan to become pregnant. It is not known if Dextroamphetamine Saccharate, Amphetamine Aspartate, Dextroamphetamine Sulfate and Amphetamine Sulfate Tablets will harm the unborn baby. Tell your healthcare provider if you or your child become pregnant during treatment with Dextroamphetamine Saccharate, Amphetamine Aspartate, Dextroamphetamine Sulfate and Amphetamine Sulfate Tablets.
- are breastfeeding or plan to breastfeed. Dextroamphetamine Saccharate, Amphetamine Aspartate, Dextroamphetamine Sulfate and Amphetamine Sulfate Tablets passes into breast milk. You or your child should not breastfeed during treatment with Dextroamphetamine Saccharate, Amphetamine Aspartate, Dextroamphetamine Sulfate and Amphetamine Sulfate Tablets. Talk to your healthcare provider about the best way to feed the baby during treatment with Dextroamphetamine Saccharate, Amphetamine Aspartate, Dextroamphetamine Sulfate and Amphetamine Sulfate Tablets.

Tell your healthcare provider about all of the medicines that you or your child take, including prescription and over-the-counter medicines, vitamins, and herbal supplements.

Dextroamphetamine Saccharate, Amphetamine Aspartate, Dextroamphetamine Sulfate and Amphetamine Sulfate Tablets and some medicines may interact with each other and cause serious side effects. Sometimes the doses of other medicines will need to be changed during treatment with Dextroamphetamine Saccharate, Amphetamine Aspartate, Dextroamphetamine Sulfate and Amphetamine Sulfate Tablets.

Your healthcare provider will decide Dextroamphetamine Saccharate, Amphetamine Aspartate, Dextroamphetamine Sulfate and Amphetamine Sulfate Tablets can be taken with other medicines.

Especially tell your healthcare provider if you or your child take:

• selective serotonin reuptake inhibitors (SSRIs)

• medicines used to treat migraine headaches called triptans

• lithium

• tramadol

• buspirone

• serotonin norepinephrine reuptake inhibitors (SNRIs)
• tricyclic antidepressants
• fentanyl
• tryptophan
• St. John’s Wort
Know the medicines that you or your child take. Keep a list of your or your child’s medicines with you to show your healthcare provider and pharmacist when you or your child get a new medicine.

Do not start any new medicine during treatment with Dextroamphetamine Saccharate, Amphetamine Aspartate, Dextroamphetamine Sulfate and Amphetamine Sulfate Tablets without talking to your healthcare provider first.

How should Dextroamphetamine Saccharate, Amphetamine Aspartate, Dextroamphetamine Sulfate and Amphetamine Sulfate Tablets be taken?

- Take Dextroamphetamine Saccharate, Amphetamine Aspartate, Dextroamphetamine Sulfate and Amphetamine Sulfate Tablets exactly as prescribed by your or your child’s healthcare provider.
- Your healthcare provider may change the dose if needed
- The first dose of the day is usually taken when you first wake up.
- Dextroamphetamine Saccharate, Amphetamine Aspartate, Dextroamphetamine Sulfate and Amphetamine Sulfate Tablets can be taken with or without food.

If you or your child take too much Dextroamphetamine Saccharate, Amphetamine Aspartate, Dextroamphetamine Sulfate and Amphetamine Sulfate Tablets, call your healthcare provider or Poison Help line at 1-800-222-1222 or go to the nearest hospital emergency room right away.

What are possible side effects of Dextroamphetamine Saccharate, Amphetamine Aspartate, Dextroamphetamine Sulfate and Amphetamine Sulfate Tablets?

Dextroamphetamine Saccharate, Amphetamine Aspartate, Dextroamphetamine Sulfate and Amphetamine Sulfate Tablets may cause serious side effects, including:

See “What is the most important information I should know about Dextroamphetamine Saccharate, Amphetamine Aspartate, Dextroamphetamine Sulfate and Amphetamine Sulfate Tablets?”

- Slowing of growth (height and weight) in children. Children should have their height and weight checked often during treatment with Dextroamphetamine Saccharate, Amphetamine Aspartate, Dextroamphetamine Sulfate and Amphetamine Sulfate Tablets. Your healthcare provider may stop your child’s Dextroamphetamine Saccharate, Amphetamine Aspartate, Dextroamphetamine Sulfate and Amphetamine Sulfate Tablets treatment if they are not growing or gaining weight as expected.

- Seizures. mainly in patients with a history of seizures. Your healthcare provider may stop treatment with Dextroamphetamine Saccharate, Amphetamine Aspartate, Dextroamphetamine Sulfate and Amphetamine Sulfate Tablets if you or your child have a seizure.

• Circulation problems in fingers and toes (peripheral vasculopathy, including Raynaud’s phenomenon).

Signs and symptoms may include:

- fingers or toes may feel numb, cool, painful
- fingers or toes may change color from pale, to blue, to red

Tell your healthcare provider if you have or your child has any numbness, pain, skin color change, or sensitivity to temperature in your fingers or toes.

Call your healthcare provider right away if you have or your child have any signs of unexplained wounds appearing on fingers or toes during treatment with Dextroamphetamine Saccharate, Amphetamine Aspartate, Dextroamphetamine Sulfate and Amphetamine Sulfate Tablets.

- Serotonin syndrome. This problem may happen when Dextroamphetamine Saccharate, Amphetamine Aspartate, Dextroamphetamine Sulfate and Amphetamine Sulfate Tablets is taken with certain other medicines. and may be life-threatening. Stop taking Dextroamphetamine Saccharate, Amphetamine Aspartate, Dextroamphetamine Sulfate and Amphetamine Sulfate Tablets and call your healthcare provider or go to the nearest hospital emergency room right away if you or your child develop any of the following signs and symptoms of serotonin syndrome:
  - Agitation, hallucination, coma
  - Fast heartbeat
  - Flushing
  - Seizure
  - Loss of coordination
  - Confusion
  - Dizziness
  - Changes in blood pressure
  - Sweating or fever
  - Nausea, vomiting, or diarrhea
  - Muscle stiffness or tightness
  - High body temperature (hyperthermia)
- New or worsening tics or worsening Tourette’s syndrome. Tell your healthcare provider if you or your child get any new or worsening tics or worsening Tourette’s syndrome during treatment with Dextroamphetamine Saccharate, Amphetamine Aspartate, Dextroamphetamine Sulfate and Amphetamine Sulfate Tablets.

The most common side effects of Dextroamphetamine Saccharate, Amphetamine Aspartate, Dextroamphetamine Sulfate and Amphetamine Sulfate Tablets include:

- stomach-ache
- decreased appetite
- nervousness

Talk to your healthcare provider if you or your child have side effects that are bothersome or do not go away. These are not all the possible side effects of Dextroamphetamine Saccharate, Amphetamine Aspartate, Dextroamphetamine Sulfate and Amphetamine Sulfate Tablets. Ask your doctor or pharmacist for more information.

Call your doctor for medical advice about side effects. You may report side effects to FDA at 1-800-FDA-1088.

How should I store Dextroamphetamine Saccharate, Amphetamine Aspartate, Dextroamphetamine Sulfate and Amphetamine Sulfate Tablets?

- Store Dextroamphetamine Saccharate, Amphetamine Aspartate, Dextroamphetamine Sulfate and Amphetamine Sulfate Tablets at room temperature, between 68 to 77°F (20 to 25°C).
- Protect Dextroamphetamine Saccharate, Amphetamine Aspartate, Dextroamphetamine Sulfate and Amphetamine Sulfate Tablets from light.
- Store Dextroamphetamine Saccharate, Amphetamine Aspartate, Dextroamphetamine Sulfate and Amphetamine Sulfate Tablets in a safe place, like a locked cabinet.
- Dispose of remaining, unused, or expired Dextroamphetamine Saccharate, Amphetamine Aspartate, Dextroamphetamine Sulfate and Amphetamine sulfate Tablets by a medicine take back program at a U.S. Drug Enforcement Administration (DEA) authorized collection site. If no takeback program or DEA authorized collector is available, mix Dextroamphetamine Saccharate, Amphetamine Aspartate, Dextroamphetamine Sulfate and Amphetamine sulfate Tablets with an undesirable, nontoxic substance such as dirt, cat litter, or used coffee grounds to make it less appealing to children and pets. Place the mixture in a container such as a sealed plastic bag and throw away Dextroamphetamine Saccharate, Amphetamine Aspartate, Dextroamphetamine Sulfate and Amphetamine sulfate Tablets in the household trash. Visit HYPERLINK "http://www.fda.gov/drugdisposal"www.fda.gov/drugdisposal for additional information on disposal of unused medicines.

Keep Dextroamphetamine Saccharate, Amphetamine Aspartate, Dextroamphetamine Sulfate and Amphetamine Sulfate Tablets and all medicines out of the reach of children.

General information about the safe and effective use of Dextroamphetamine Saccharate, Amphetamine Aspartate, Dextroamphetamine Sulfate and Amphetamine Sulfate Tablets.

Medicines are sometimes prescribed for purposes other than those listed in a Medication Guide. Do not use Dextroamphetamine Saccharate, Amphetamine Aspartate, Dextroamphetamine Sulfate and Amphetamine Sulfate Tablets for a condition for which it was not prescribed. Do not give Dextroamphetamine Saccharate, Amphetamine Aspartate, Dextroamphetamine Sulfate and Amphetamine Sulfate Tablets to other people, even if they have the same condition. It may harm them and it is against the law. You can ask your healthcare provider or pharmacist for information about Dextroamphetamine Saccharate, Amphetamine Aspartate, Dextroamphetamine Sulfate and Amphetamine Sulfate Tablets that is written for healthcare professionals.

What are the ingredients in Dextroamphetamine Saccharate, Amphetamine Aspartate, Dextroamphetamine Sulfate and Amphetamine Sulfate Tablets?

Active Ingredients: dextroamphetamine saccharate, amphetamine aspartate, dextroamphetamine sulfate, and amphetamine sulfate

Inactive Ingredients: Colloidal silicon dioxide, magnesium stearate, microcrystalline cellulose, povidone, and pregelatinized starch; The 5 mg, 7.5 mg, and 10 mg tablets contain the color additive FD&C Blue#1 aluminum lake; The 12.5 mg, 15 mg, 20 mg, and 30 mg tablets contain the color additive FD&C Yellow#6 aluminum lake.

Distributed by:

Aurobindo Pharma USA, Inc
279 Princeton-Hightstown Road East Windsor, NJ-08520

Dispense with Medication Guide available at http://www.aurobindous a.com/product-medication- guides

For more information about Dextroamphetamine Saccharate, Amphetamine Aspartate, Dextroamphetamine Sulfate and Amphetamine Sulfate Tablets, please contact Aurobindo Pharma USA, Inc at 1-866-850-2876

This Medication Guide has been approved by the U.S. Food and Drug Administration.

Revised: 02/2025

PACKAGE LABEL.PRINCIPAL DISPLAY PANEL 5mg (100ct bottle)

NDC 16714-948-01
Dextroamphetamine Saccharate,Amphetamine
Aspartate,Dextroamphetamine Sulfate and
Amphetamine Sulfate Tablets
(Mixed Salts of a Single Entity Amphetamine Product)
5 mg
Pharmacist: Please dispense with Medication Guide
provided separately.
Rx only 100 Tablets

PACKAGE LABEL.PRINCIPAL DISPLAY PANEL 7.5 mg (100ct bottle)

NDC 16714-949-01

Dextroamphetamine Saccharate, Amphetamine Aspartate, Dextroamphetamine Sulfate and Amphetamine Sulfate Tablets
(Mixed Salts of a Single Entity Amphetamine Product)
7.5 mg
Pharmacist: Please dispense with Medication Guide provided separately.
Rx only 100 Tablets

PACKAGE LABEL.PRINCIPAL DISPLAY PANEL 10 mg (100ct bottle)

NDC 16714-950-01
Dextroamphetamine Saccharate, Amphetamine Aspartate, Dextroamphetamine Sulfate and Amphetamine Sulfate Tablets
(Mixed Salts of a Single Entity Amphetamine Product)
10 mg
Pharmacist: Please dispense with Medication Guide provided separately.
Rx only 100 Tablets

PACKAGE LABEL.PRINCIPAL DISPLAY PANEL 15 mg (100ct bottle)

NDC 16714-952-01
Dextroamphetamine Saccharate, Amphetamine Aspartate, Dextroamphetamine Sulfate and
Amphetamine Sulfate Tablets
(Mixed Salts of a Single Entity Amphetamine Product)
15 mg
Pharmacist: Please dispense with Medication Guide provided separately.
Rx only 100 Tablets

PACKAGE LABEL.PRINCIPAL DISPLAY PANEL 20 mg (100ct bottle)

NDC 16714-953-01
Dextroamphetamine Saccharate, Amphetamine Aspartate, Dextroamphetamine Sulfate and Amphetamine Sulfate Tablets
(Mixed Salts of a Single Entity Amphetamine Product)
20 mg
Pharmacist: Please dispense with Medication Guide provided separately.
Rx only 100 Tablets

PACKAGE LABEL.PRINCIPAL DISPLAY PANEL 30mg (100ct bottle)

NDC 16714-954-01
Dextroamphetamine Saccharate, Amphetamine Aspartate, Dextroamphetamine Sulfate and Amphetamine Sulfate Tablets
(Mixed Salts of a Single Entity Amphetamine Product)
30 mg
Pharmacist: Please dispense with Medication Guide provided separately.
Rx only 100 Tablets